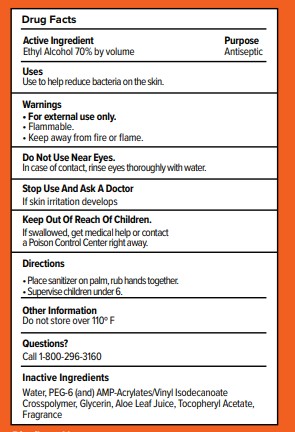 DRUG LABEL: Moxe Citrus Splash Hand Sanitizer
NDC: 84004-001 | Form: GEL
Manufacturer: Premark Health Science
Category: otc | Type: HUMAN OTC DRUG LABEL
Date: 20250430

ACTIVE INGREDIENTS: ALCOHOL 70 mL/100 mL
INACTIVE INGREDIENTS: MANDARIN OIL; ALOE; .ALPHA.-TOCOPHEROL ACETATE, DL-; CARBOMER HOMOPOLYMER, UNSPECIFIED TYPE; GLYCERIN; WATER

Moxe Citrus Splash Hand Sanitizer